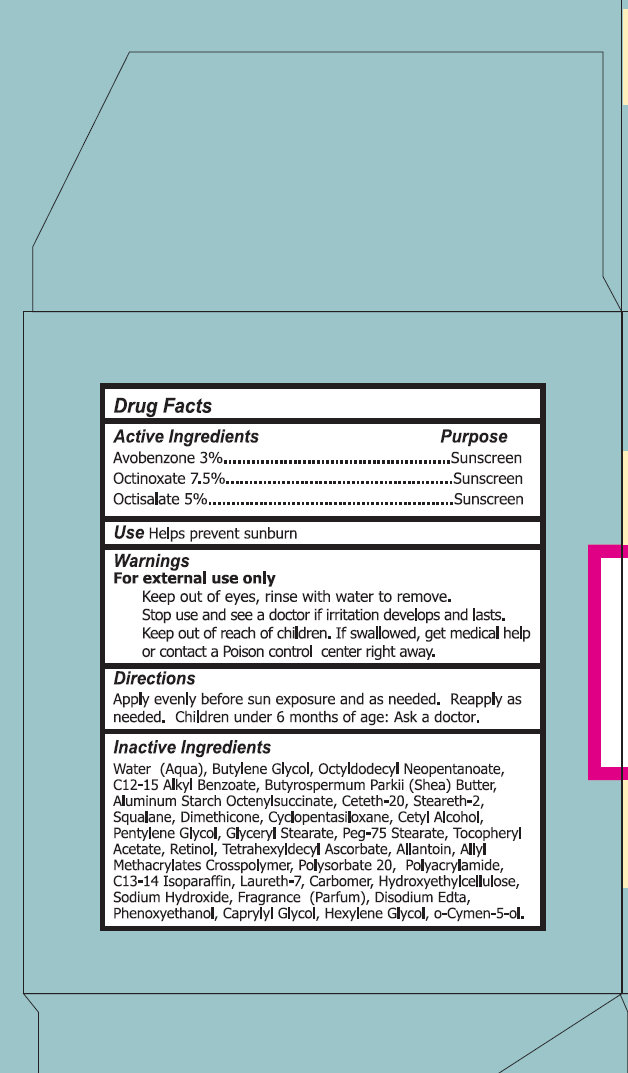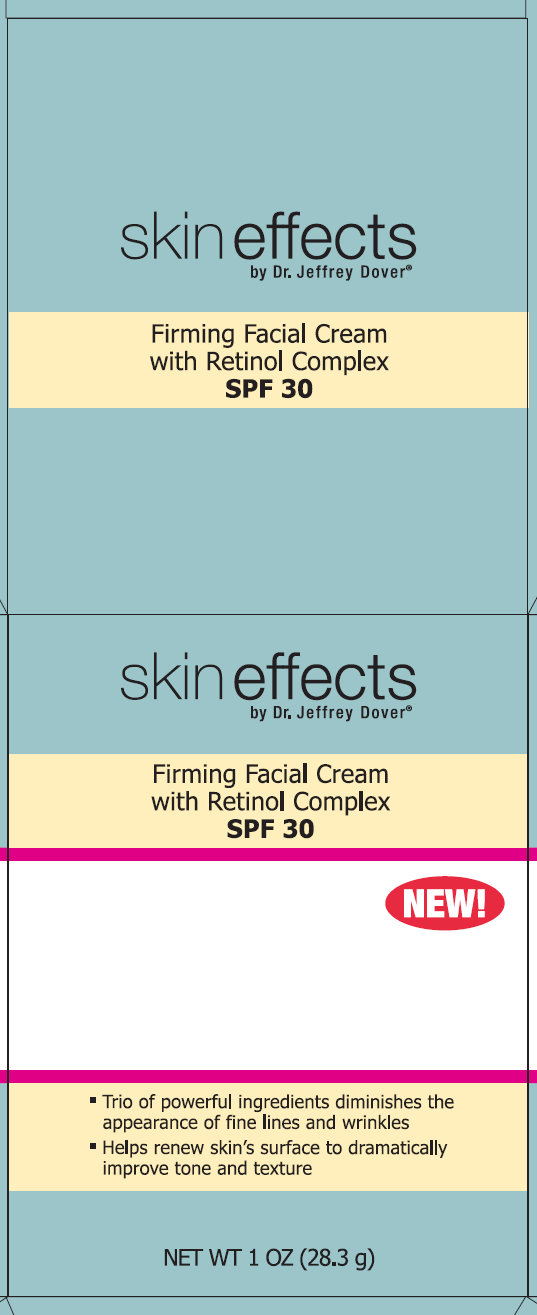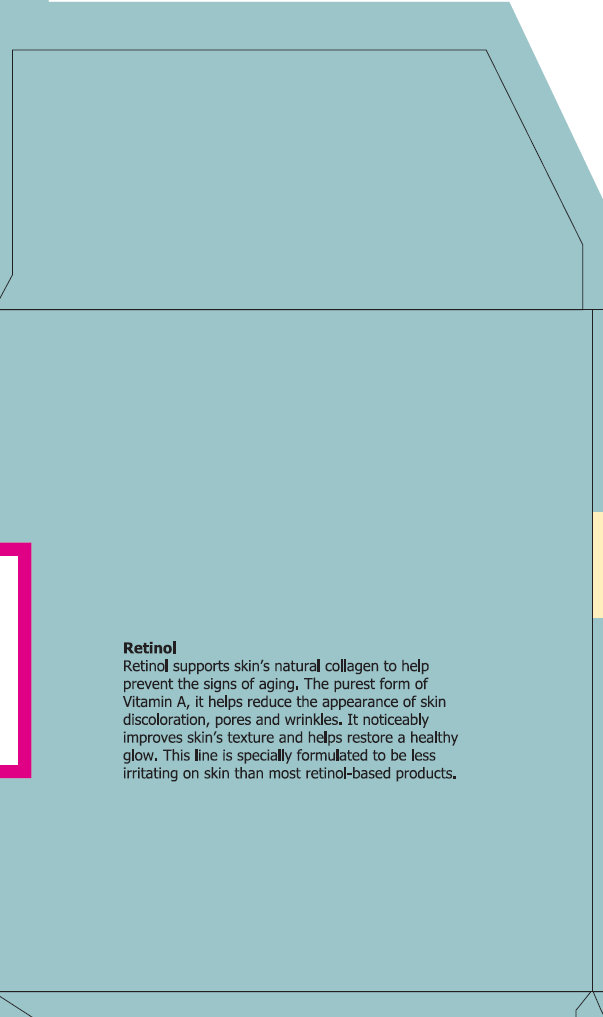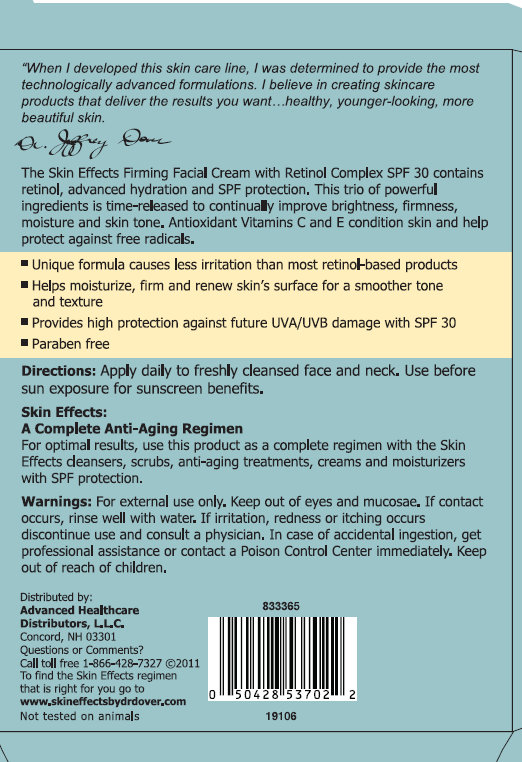 DRUG LABEL: skin effects Firming Facial with Retinol Complex SPF 30
NDC: 42877-001 | Form: CREAM
Manufacturer: Diversified Global Technologies DBA Diversified Distribution
Category: otc | Type: HUMAN OTC DRUG LABEL
Date: 20111012

ACTIVE INGREDIENTS: AVOBENZONE 3 g/100 g; OCTINOXATE 7.5 g/100 g; OCTISALATE 5 g/100 g
INACTIVE INGREDIENTS: WATER; BUTYLENE GLYCOL; OCTYLDODECYL NEOPENTANOATE; ALKYL (C12-15) BENZOATE; SHEA BUTTER; ALUMINUM STARCH OCTENYLSUCCINATE; CETETH-20; STEARETH-2; SQUALANE; DIMETHICONE; CYCLOMETHICONE 5 ; CETYL ALCOHOL; PENTYLENE GLYCOL; GLYCERYL MONOSTEARATE; PEG-75 STEARATE; .ALPHA.-TOCOPHEROL ACETATE, D- ; RETINOL; TETRAHEXYLDECYL ASCORBATE; ALLANTOIN; POLYSORBATE 20; C13-14 ISOPARAFFIN; LAURETH-7; SODIUM HYDROXIDE; EDETATE DISODIUM; PHENOXYETHANOL; CAPRYLYL GLYCOL; HEXYLENE GLYCOL; O-CYMEN-5-OL

skin effects Firming Facial Cream with Retinol Complex SPF 30

Active Ingredients

Avobenzone 3%

Octinoxate 7.5%

Octisalate 5%

Purpose

Sunscreen

Use

Helps prevent sunburn

Warnings

For external use only

Keep out of eyes, rinse with water to remove.

Stop use and see a doctor if irritation develops and lasts.

Keep out of reach of children. If swallowed, get medical help or contact a Poison Control center right away.

Directions

Apply evenly before sun exposure and as needed.

Reapply as needed.

Children under 6 months of age: Ask a doctor.

Inactive Ingredients

Water (Aqua), Butylene Glycol, Octyldodecyl Neopentanoate, C12-15 Alkyl Benzoate, Butyrospermum Parkii (Shea) Butter, Aluminum Starch Octenylsuccinate, Ceteth-20, Steareth-2, Squalane, Dimethicone, Cyclopentasiloxane, Cetyl Alcohol, Pentylene Glycol, Glyceryl Stearate, PEG-75 Stearate, Tocopheryl Acetate, Retinol, Tetrahexyldecyl Ascorbate, Allantoin, Allyl Methacrylates Crosspolymer, Polysorbate 20, Polyacrylamide, C13-14 Isoparaffin, Laureth-7, Carbomer, Hydroxyethylcellulose, Sodium Hydroxide, Fragrance (Parfum), Disodium EDTA, Phenoxyethanol, Caprylyl Glycol, Hexylene Glycol, O-Cymen-5-Ol.

Retinol

Retinol supports skin's natural collagen to help prevent the signs of aging. The purest form of Vitamin A, it helps reduce the appearance of skin discoloration, pores and wrinkles. It noticeably improves skin's texture and helps restore a healthy glow. This line is specially formulated to be less irritating than most retinol-based products.

Skin Effects Firming Facial Cream with Retinol Complex SPF 30

"When I developed this skin care line, I was determined to provide the most technologically advanced formulations. I believe in creating skin care products that deliver the results you want, healthy, younger-looking, more beautiful skin." Dr. Jeffrey Dover
The Skin Effects Firming Facial Cream with Retinol Complex SPF 30 contains retinol, advanced hydration and SPF protection. This trio of powerful ingredients is time-released to improve brightness, firmness, moisture and skin tone. Antioxidant Vitamins C and E condition skin and help protect against free radicals.

- Unique formula causes less irritation than most retinol-based products
- Helps moisturize, firm and renew skin's surface for a smoother tone and texture
- Provides high protection against future UVA/UVB damage with SPF 30
- Paraben free

Directions:

Apply daily to freshly cleansed face and neck. Use before sun exposure for sunscreen benefits.

Skin Effects: A Complete Anti-Aging Regimen

For optimal results, use this product as a complete regimen with the Skin Effects cleansers, scrubs, anti-aging treatments, creams and moisturizes with SPF protection.

Warnings:

For external use only. Keep out of eyes and mucosa. If contact occurs, rinse well with water. If irritation, redness or itching occurs discontinue use and consult a physician. In case of accidental ingestion, get professional assistance or contact a Poison Control Center immediately. Keep out of reach of children. For external use only. Keep out of eyes, rinse with water to remove. Stop use and see a doctor if irritation develops and lasts. Keep out of reach of children.

Distributed by:

Advanced Healthcare Distributors, L.L.C.

Concord, NH 03301

Questions or Comments?

Call Toll Free 1-866-428-7327

To find the Skin Effects regimen that is right for you go to

www.skineffectsbydrdover.com

Not tested on animals

skin effects Firming Facial Cream with Retinol Complex SPF 30 1oz / 28.3g

skin effects

by Dr. Jeffrey Dover

Firming Facial Cream with Retinol Complex SPF 30

- Trio of powerful ingredients diminishes the appearance of fine lines and wrinkles
- Helps renew skin's surface to dramatically improve tone and texture

NET WT 1 OZ (28.3g)